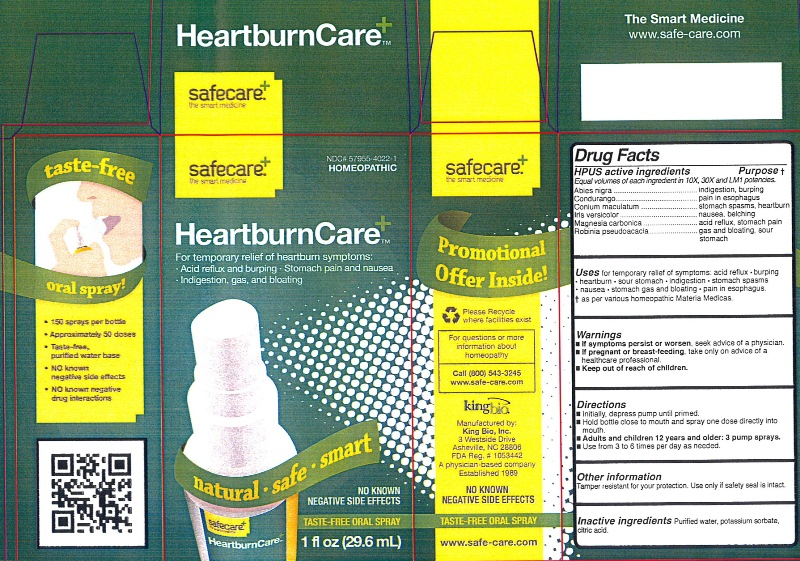 DRUG LABEL: HeartburnCare
NDC: 57955-4022 | Form: LIQUID
Manufacturer: King Bio Inc.
Category: homeopathic | Type: HUMAN OTC DRUG LABEL
Date: 20120613

ACTIVE INGREDIENTS: PICEA MARIANA RESIN 10 [hp_X]/29.6 mL; MARSDENIA CONDURANGO BARK 10 [hp_X]/29.6 mL; CONIUM MACULATUM FLOWERING TOP 10 [hp_X]/29.6 mL; IRIS VERSICOLOR ROOT 10 [hp_X]/29.6 mL; MAGNESIUM CARBONATE 10 [hp_X]/29.6 mL; ROBINIA PSEUDOACACIA BARK 10 [hp_X]/29.6 mL
INACTIVE INGREDIENTS: WATER; POTASSIUM SORBATE; CITRIC ACID MONOHYDRATE

HeartburnCare

Active Ingredients

HPUS active ingredients

Equal volumes of each ingredient in 10X, 30X and LM1 potencies.

Abies nigra, Condurango, Conium maculatum, Iris versicolor, Magnesia carbonica and Robinia pseudoacacia.

Reference image heartburncare.jpg

Inactive Ingredients

Purified water, potassium sorbate and citric acid.

Reference image heartburncare.jpg

Purpose

HPUS active ingredients Purpose

Equal volumes of each ingredient in 10X, 30X and LM1 potencies.

Abies nigra...............................................................indigestion, burping

Condurango.............................................................pain in esophagus

Conium maculatum...................................................stomach spasms, heartburn

Iris versicolor...........................................................nausea, belching

Magnesia carbonica.................................................acid reflux, stomach pain

Robinia pseudoacacia..............................................gas and bloating, sour stomach

Reference image heartburncare.jpg

Indications and Usage

Uses for temporary relief of symptoms:

- acid reflux
- burping
- heartburn
- sour stomach
- indigestion
- stomach spasms
- nausea
- stomach gas and bloating
- pain in esophagus

as per various homeopathic Materia Medicas.
Reference image heartburncare.jpg

Warnings

- If symptoms persist or worsen, seek advice of a physician.
- If pregnant or breast-feeding, take only on advice of a healthcare professional.
- Keep out of reach of children.

Other information:
Tamper resistant for your protection. Use only if safety seal is intact.
Reference image heartburncare.jpg

Dosage and Administration

Directions:

- Initially, depress pump until primed.
- Hold bottle close to mouth and spray one dose directly into mouth.
- Adults and children 12 years and older: 3 pump sprays.
- Use from 3 to 6 times per day as needed.

Reference image heartburncare.jpg

Keep out of reach of children.

Reference image heartburncare.jpg

PACKAGE LABEL

King Bio Inc.

3 Westside Drive

Asheville, NC 28806

For questions or more information about homeopathy call 800-543-3245 or www.safe-care.com